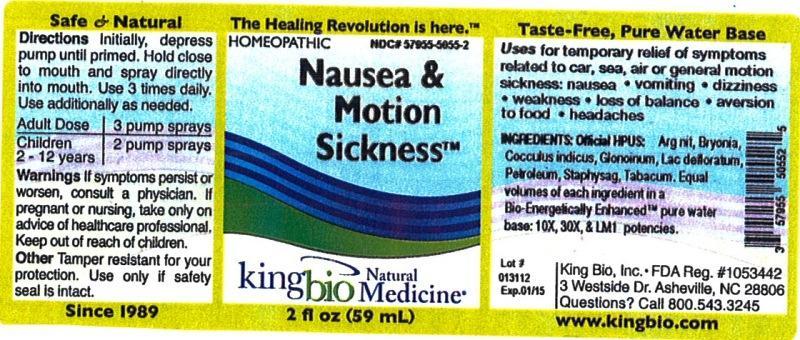 DRUG LABEL: Nausea and Motion Sickness
NDC: 57955-5055 | Form: LIQUID
Manufacturer: King Bio Inc.
Category: homeopathic | Type: HUMAN OTC DRUG LABEL
Date: 20120904

ACTIVE INGREDIENTS: SILVER NITRATE 10 [hp_X]/59 mL; BRYONIA ALBA ROOT 10 [hp_X]/59 mL; ANAMIRTA COCCULUS SEED 10 [hp_X]/59 mL; NITROGLYCERIN 10 [hp_X]/59 mL; SKIM MILK 10 [hp_X]/59 mL; KEROSENE 10 [hp_X]/59 mL; DELPHINIUM STAPHISAGRIA SEED 10 [hp_X]/59 mL; TOBACCO LEAF 10 [hp_X]/59 mL
INACTIVE INGREDIENTS: WATER

Nausea and Motion Sickness

Active Ingredients

Official HPUS: Argentum nitricum, Bryonia, Cocculus indicus, Glonoinum, Lac defloratum, Petroleum, Staphysagria and Tabacum.

Inactive Ingredient

Equal volumes of each ingredient in a Bio-Energetically Enhanced pure water base: 10X, 30X, and LM1 potencies.

Purpose

Uses for temporary relief of symptoms related to car, sea, air or general motion sickness:

- nausea, vomiting, dizziness
- weakness
- loss of balance
- aversion to food
- headaches

Dosage and Administration

Directions initially, depress pump until primed. Hold close to mouth and spray directly into mouth. Use 3 times daily. Use additionally as needed.

Adult Dose 3 pump sprays

Children 2 - 12 years 2 pump sprays

Warnings

If symptoms persist or worsen, consult a physician. If pregnant or nursing, take only on advice of healthcare professional. Keep out of reach of children.

Other: Tamper resistant for your protection. Use only if safety seal is intact.

Keep out of reach of children.

Indication and Usage

Uses for temporary relief of symptoms related to car, sea, air or general motion sickness: nausea, vomiting, dizziness, weakness, loss of balance, aversion to food, headaches.

PACKAGE LABEL

King Bio, Inc

3 Westside Drive

Asheville, NC 28806

Question? Call 800.543.3245

www.kingbio.com